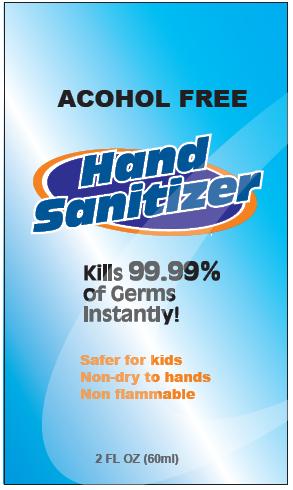 DRUG LABEL: ALCOHOL FREE HAND SANITIZER
NDC: 31190-100 | Form: AEROSOL, FOAM
Manufacturer: Shanghai Kejing Cleaning Products Co., Ltd.
Category: otc | Type: HUMAN OTC DRUG LABEL
Date: 20100407

ACTIVE INGREDIENTS: BENZALKONIUM CHLORIDE 0.13 mL/100 mL
INACTIVE INGREDIENTS: WATER; COCAMIDOPROPYL BETAINE; PROPYLENE GLYCOL; GLYCERIN; CITRIC ACID MONOHYDRATE; TROLAMINE

ALCOHOL FREE HAND SANITIZER

Active Ingredient Purpose

Benzalkonium Chloride 0.13percent......Antimicrobial

PURPOSE

Use: To decrease bacterial on the skin that could cause disease. Recommended for repeated use.

Warnings

For external use only.

Avoid contact with eyes. In case of contact with eyes, flush thoroughly with water.

Stop use and ask doctor if skin irritation develops.

Keep out of reach of children. If swallowed, get medical help or contact a Poison Control Center immediately.

Directions

For adults and children 2 yrs. and older. Apply a thumbnail size amount on palms and rub hands thoroughly until dry.

Other Information:

Do not freeze.

INACTIVE INGREDIENT

Inactive Ingredients: Water, Cocamidopropyl Betaine, Propylene Glycol, Glycerine, Citric Acid, Cocamidopropylamine Oxide, Triethanolamine (TEA)

DEPENDENCE

Distributed by Tekweld Inc.
180 Central Avenue
FARMINGDALE, NY 11735

Made in China

PACKAGE LABEL

ALCOHOL FREE

Hand Sanitizer

Kills 99.99 percent of Germs Instantly!

Safer for kids, Non-dry to hands, Non flammable